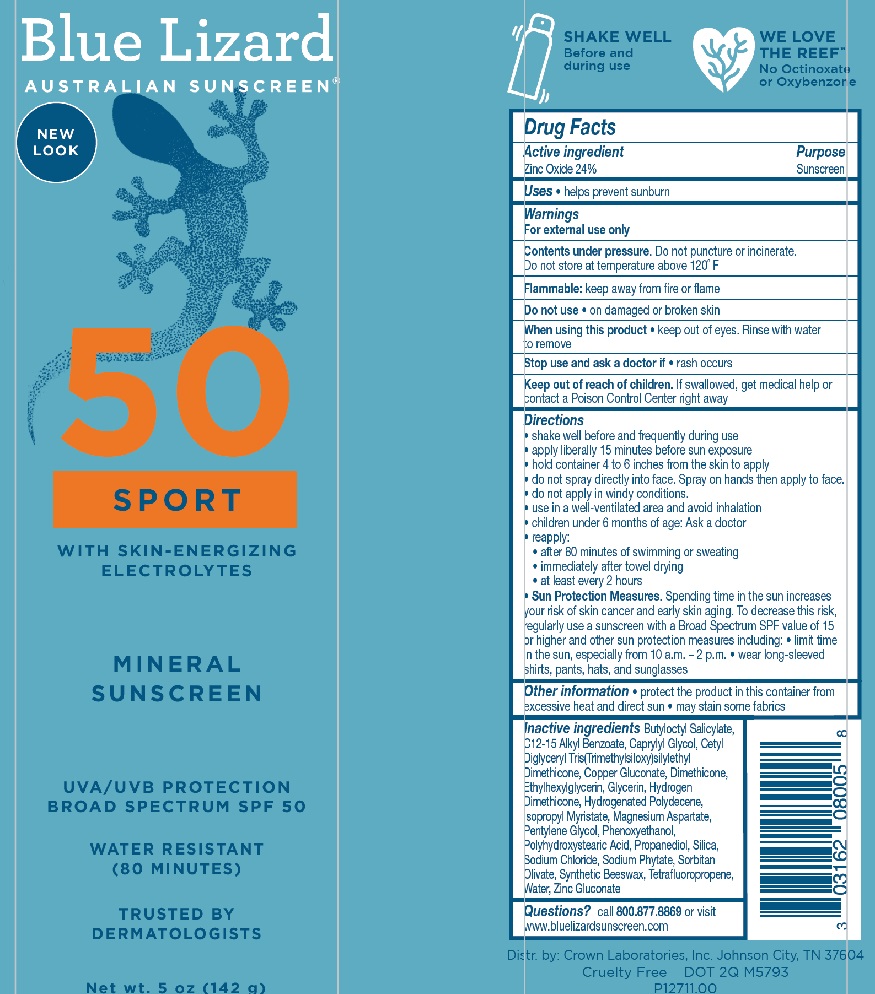 DRUG LABEL: Blue Lizard Sport SPF 50
NDC: 0316-2080 | Form: SPRAY
Manufacturer: Crown Laboratories
Category: otc | Type: HUMAN OTC DRUG LABEL
Date: 20260112

ACTIVE INGREDIENTS: ZINC OXIDE 24 mg/1 g
INACTIVE INGREDIENTS: ETHYLHEXYLGLYCERIN; DIMETHICONE; HYDROGENATED POLY(C6-14 OLEFIN; 4 CST); PHYTATE SODIUM; CETYL DIGLYCERYL TRIS(TRIMETHYLSILOXY)SILYLETHYL DIMETHICONE (3500 MM2/S); ALKYL (C12-15) BENZOATE; ISOPROPYL MYRISTATE; MAGNESIUM ASPARTATE; SODIUM CHLORIDE; WATER; COPPER GLUCONATE; HYDROGEN DIMETHICONE (20 CST); SYNTHETIC BEESWAX; SORBITAN OLIVATE; ZINC GLUCONATE; PHENOXYETHANOL; CAPRYLYL GLYCOL; BUTYLOCTYL SALICYLATE; POLYHYDROXYSTEARIC ACID (2300 MW); 1,3,3,3-TETRAFLUOROPROPENE, (1E)-; GLYCERIN; PENTYLENE GLYCOL; SILICON DIOXIDE; PROPANEDIOL

Blue Lizard Sport SPF 50 Sunscreen Spray

Active ingredients

Zinc Oxide 24%

Purpose

Sunscreen

Uses

- helps prevent sunburn

Warnings

For external use only

Contents under pressure. Do not puncture or incinerate. Do not store at temperature above 120 ˚F

Flammable: keep away from fire or flame

Do not use • on damaged or broken skin

When using this product • keep out of eyes. Rinse with water to remove

Stop use and ask doctor if • rash occurs

Keep out of reach of children. If swallowed, get medical help or contact a Poison Control Center right away

Do not use

- on damaged or broken skin

When using this product

- keep out of eyes. Rinse with water to remove

Stop use and ask a doctor if

- rash occurs

Keep out of reach of children.

If swallowed, get medical help or contact a Poison Control Center right away

Directions

• shake well before and frequently during use

• apply liberally 15 minutes before sun exposure

• hold container 4 to 6 inches from the skin to apply

• do not spray directly into face. Spray on hands then apply to face.

• do not apply in windy conditions.

• use in a well-ventilated area and avoid inhalation

• children under 6 months of age: Ask a doctor

• Sun Protection Measures. Spending time in the sun increases your risk of skin cancer and early skin aging. To decrease this risk, regularly use a sunscreen with a Broad Spectrum SPF value of 15 or higher and other sun protection measures including: • limit time in the sun, especially from 10 a.m.- 2 p.m. • wear long-sleeved shirts, pants, hats, and sunglasses

• reapply:

• after 80 minutes of swimming or sweating

• immediately after towel drying

• at least every 2 hours

Other information

- protect the product in this container from excessive heat and direct sun
- may stain some fabrics

Inactive ingredients

Butyloctyl Salicylate, C12-15 Alkyl Benzoate, Caprylyl Glycol, Cetyl Diglyceryl Tris(Trimethylsiloxy)silylethyl Dimethicone, Copper Gluconate, Dimethicone, Ethylhexylglycerin, Glycerin, Hydrogen Dimethicone, Hydrogenated Polydecene, Isopropyl Myristate, Magnesium Aspartate, Pentylene Glycol, Phenoxyethanol, Polyhydroxystearic Acid, Propanediol, Silica, Sodium Chloride, Sodium Phytate, Sorbitan Olivate, Synthetic Beeswax, Tetrafluoropropene, Water, Zinc Gluconate

Questions?

Call 800.877.8869 or visit www.bluelizardsunscreen.com

Blue Lizard Sport SPF 50 Spray 5 oz Label

BLUE LIZARD

AUSTRALIAN SUNSCREEN

50

SPORT

with skin-energizing electrolytes

MINERAL SUNSCREEN

UVA/UVB PROTECTION

BROAD SPECTRUM SPF 50

WATER RESISTANT (80 MINUTES)

TRUSTED BY DERMATOLOGISTS

Net wt. 5 oz (142 g)